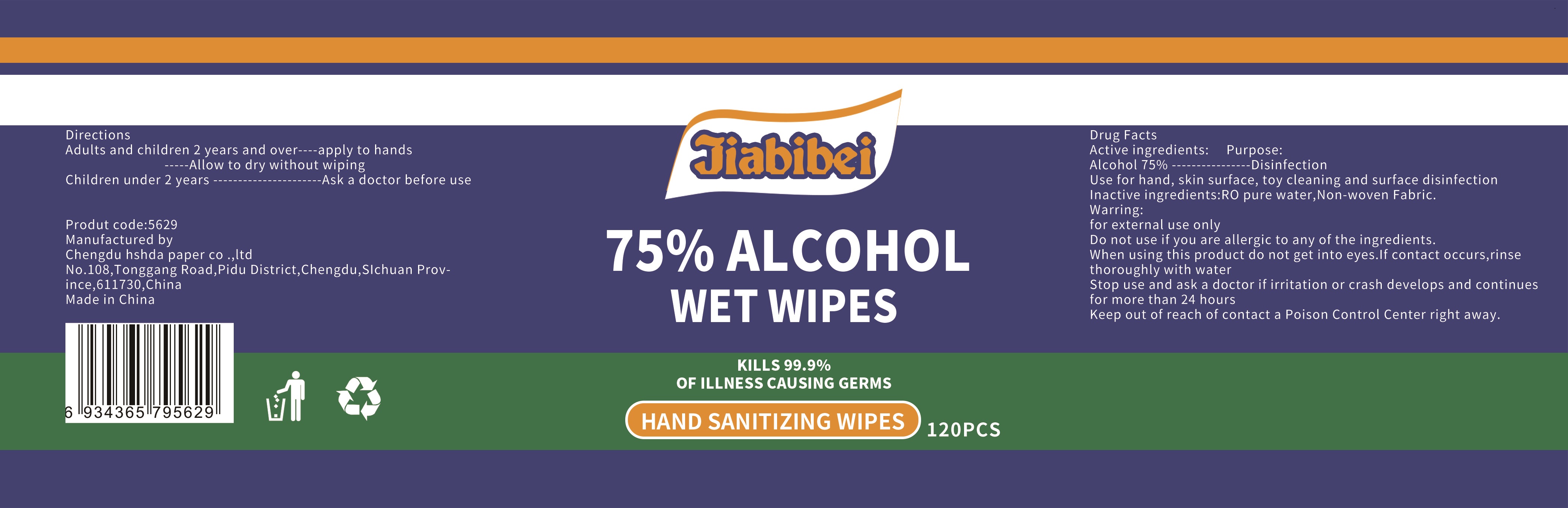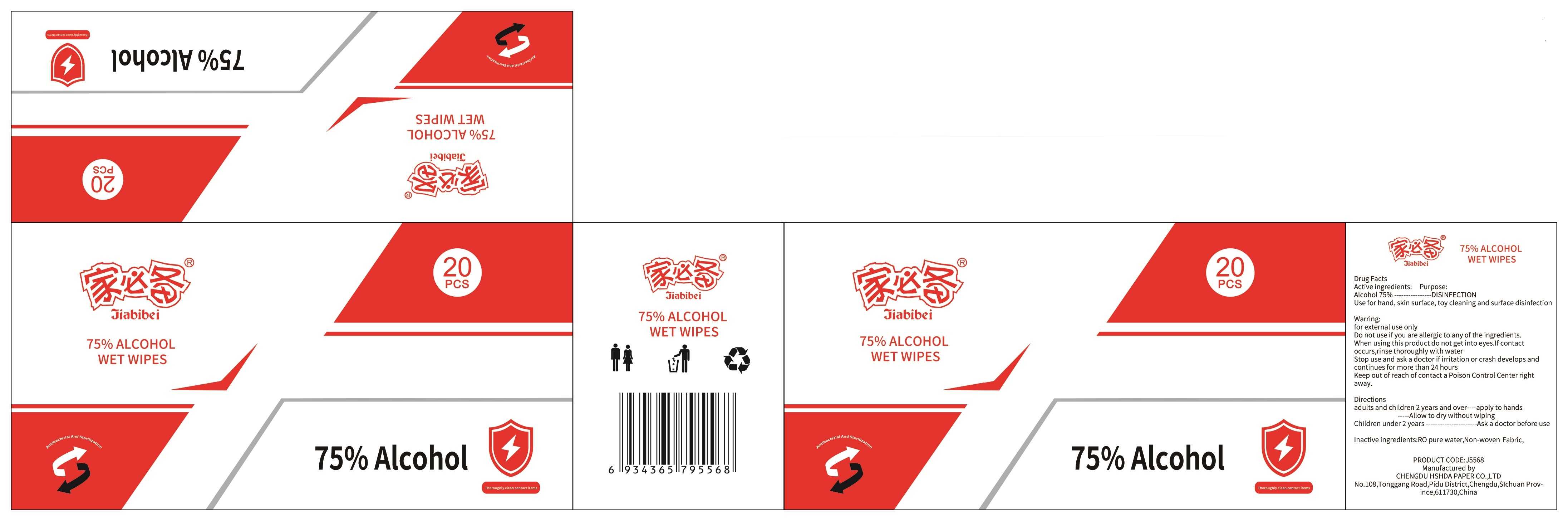 DRUG LABEL: Jiabibei 75% Alcohol Wet Wipes
NDC: 80617-001 | Form: CLOTH
Manufacturer: Chengdu Hshda Paper Co., Ltd.
Category: otc | Type: HUMAN OTC DRUG LABEL
Date: 20200918

ACTIVE INGREDIENTS: ALCOHOL 75 mL/100 1
INACTIVE INGREDIENTS: WATER

80617-001
Jiabibei 75% Alcohol Wet Wipes

Active Ingredient(s)

Alcohol 75%

Purpose

DISINFECTION

Use

Use for hand, skin surface, toy cleaning and surface disinfection

Warnings

or external use only

Do not use if you are allergic to any of the ingredients.

When using this product do not get into eyes.If contact occurs,rinse thoroughly with water

Stop use and ask a doctor if irritation or crash develops and continues for more than 24 hours

Keep out of reach of contact a Poison Control Center right away.

Do not use if you are allergic to any of the ingredients.

When using this product do not get into eyes.If contact occurs,rinse thoroughly with water

Stop use and ask a doctor if irritation or crash develops and continues for more than 24 hours

Keep out of reach of contact a Poison Control Center right away.

Stop use and ask a doctor if irritation or crash develops and continues for more than 24 hours

KEEP OUT OF REACH OF CHILDREN

Keep out of reach of contact a Poison Control Center right away.

Directions

adults and children 2 years and over----apply to hands-----Allow to dry without wiping
Children under 2 years ----------------------Ask a doctor before use

Other information

/

Inactive ingredients

RO pure water, Non-woven Fabric.